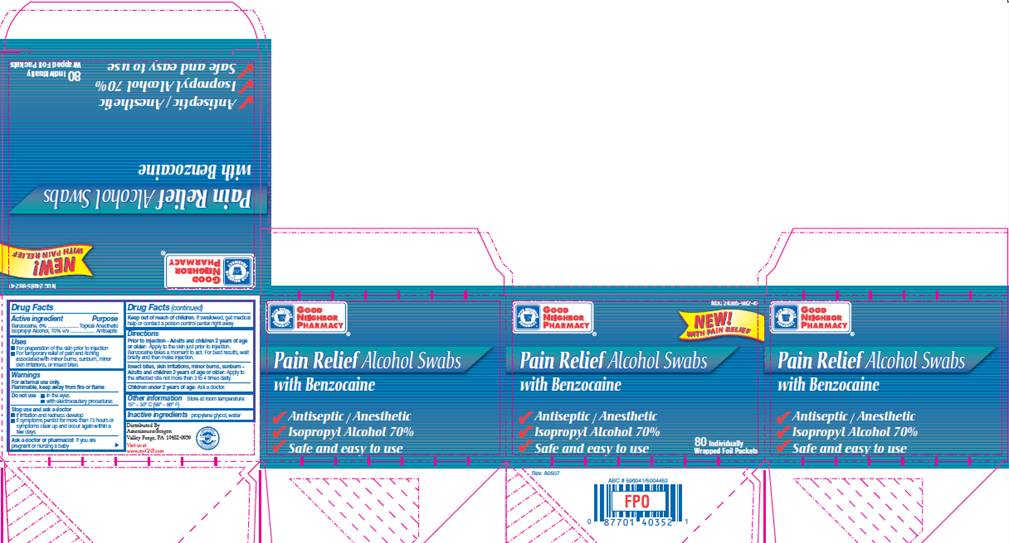 DRUG LABEL: Pain Relief Alcohol Swabs
NDC: 24385-982 | Form: SWAB
Manufacturer: Amerisource Bergen
Category: otc | Type: HUMAN OTC DRUG LABEL
Date: 20100104

ACTIVE INGREDIENTS: benzocaine 0.06 mL/1 1; isopropyl alcohol 0.70 mL/1 1
INACTIVE INGREDIENTS: propylene glycol; water

DRUG FACTS

ACTIVE INGREDIENTS

Benzocaine 6%
Isopropyl alcohol 70% v/v

PURPOSE

Topical Anesthetic

Antiseptic

USES

- For preparation of the skin prior to injection
- For temporary relief of pain and itching associated with minor burns, sunburn, minor skin irritations, or insect bites

WARNINGS

For external use only.
Flammable, keep away from fire or flame.

Do not use

- in the eyes
- with electrocautery procedures

Stop use and ask a doctor

- if irritation and redness develop
- if symptoms persist for more than 72 hours or symptoms clear up and occur within a few days.

Ask a doctor or pharmacist

if you are pregnant or nursing a baby.

Keep out of reach of children

If swallowed, get medical help or contact a Poison Control Center right away.

DIRECTIONS

Prior to Injection - Adults and children 2 years of age or older:
Apply to the skin just prior to injection. Benzocaine takes a minute to act. for best results, wait briefly and then make injection.
Insect bites, skin irritations, minor burns, sunburn -
Adults and children 2 years of age or older:
Apply to the affected site not more than 3 to 4 times daily.
Children under 2 years of age: Ask a doctor.

OTHER INFORMATION

Store at room temperature: 15° - 30° C (59° - 86° F)

INACTIVE INGREDIENTS

propylene glycol, purified water

CARTON INFORMATION

NDC 124385-982-41

GOOD NEIGHBOR PHARMACY

Pain Relief Alcohol Swabs
with Benzocaine

Antiseptic / Anesthetic
Isopropyl Alcohol 70%
Safe and easy to use

80 Individually Wrapped Foil Packets
Distributed by
AmerisourceBergen
Valley Forge, PA 19482-0959
Visit us at www.myGNP.com